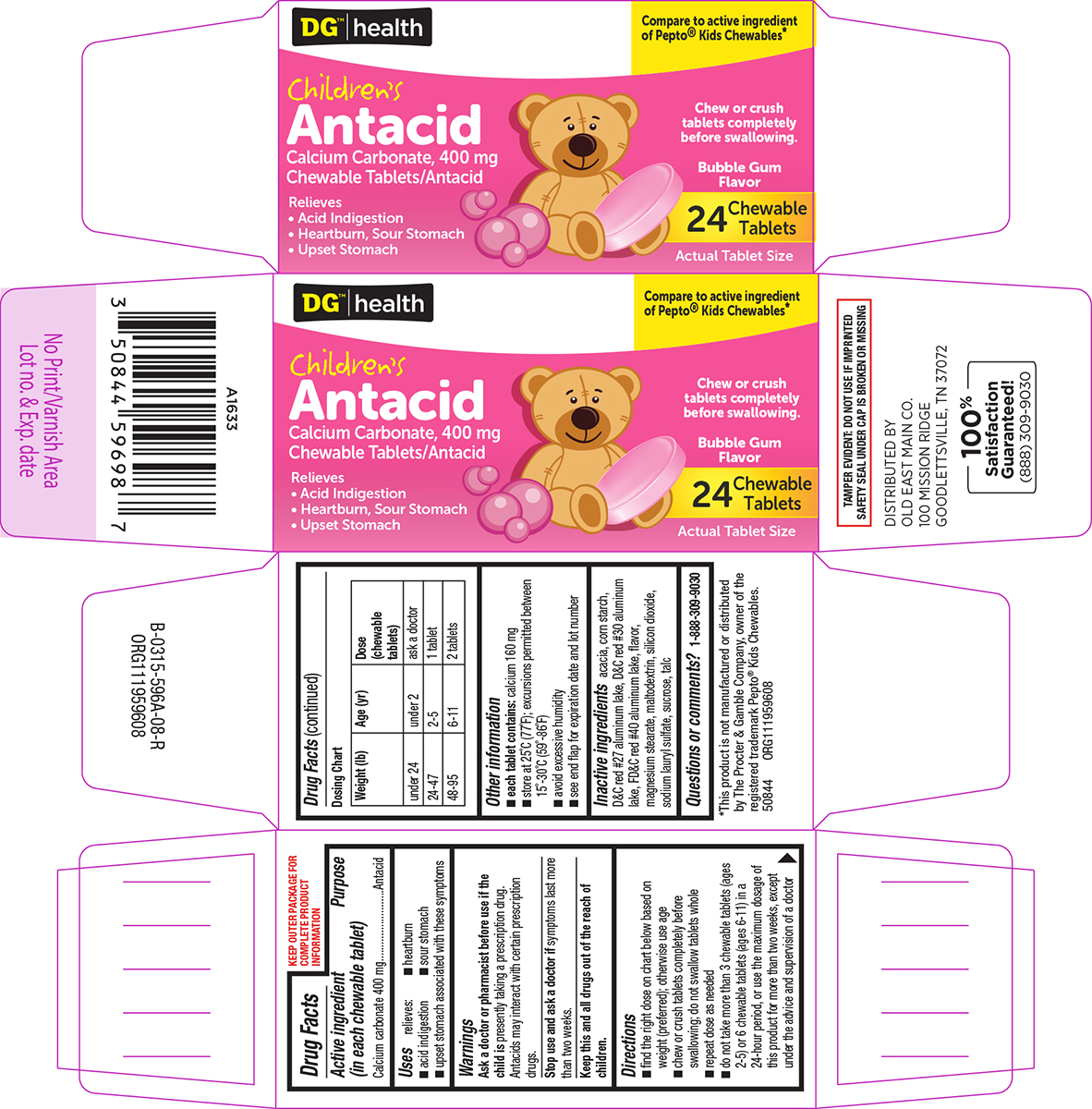 DRUG LABEL: Childrens Antacid
NDC: 55910-590 | Form: TABLET, CHEWABLE
Manufacturer: DOLGENCORP, LLC
Category: otc | Type: HUMAN OTC DRUG LABEL
Date: 20250607

ACTIVE INGREDIENTS: CALCIUM CARBONATE 400 mg/1 1
INACTIVE INGREDIENTS: ACACIA; STARCH, CORN; D&C RED NO. 27 ALUMINUM LAKE; D&C RED NO. 30 ALUMINUM LAKE; FD&C RED NO. 40 ALUMINUM LAKE; MAGNESIUM STEARATE; MALTODEXTRIN; SILICON DIOXIDE; SODIUM LAURYL SULFATE; SUCROSE; TALC

Dollar General 44-596A

Active ingredient (in each chewable tablet)

Calcium carbonate 400 mg

Purpose

Antacid

Uses

relieves:

- heartburn
- acid indigestion
- sour stomach
- upset stomach associated with these symptoms

Warnings

Ask a doctor or pharmacist before use if the child is

presently taking a prescription drug. Antacids may interact with certain prescription drugs.

Stop use and ask a doctor if

symptoms last more than two weeks.

Directions

- find the right dose on chart below based on weight (preferred); otherwise use age
- chew or crush tablets completely before swallowing; do not swallow tablets whole
- repeat dose as needed
- do not take more than 3 chewable tablets (ages 2-5) or 6 chewable tablets (ages 6-11) in a 24-hour period, or use the maximum dosage of this product for more than two weeks, except under the advice and supervision of a doctor

Dosing Chart

Weight (lb) | Age (yr) | Dose (chewable tablets)
under 24 | under 2 | ask a doctor
24-47 | 2-5 | 1 tablet
48-95 | 6-11 | 2 tablets

Other information

- each tablet contains: calcium 160 mg
- store at 25°C (77°F); excursions permitted between 15°-30°C (59°-86°F)
- avoid excessive humidity
- see end flap for expiration date and lot number

Inactive ingredients

acacia, corn starch, D&C red #27 aluminum lake, D&C red #30 aluminum lake, FD&C red #40 aluminum lake, flavor, magnesium stearate, maltodextrin, silicon dioxide, sodium lauryl sulfate, sucrose, talc

Questions or comments?

1-888-309-9030

Principal display panel

DG™ | health

Compare to active ingredient
of Pepto® Kids Chewables*

Children's
Antacid
Calcium Carbonate, 400 mg
Chewable Tablets/Antacid

Relieves
• Acid Indigestion
• Heartburn, Sour Stomach
• Upset Stomach

Chew or crush
tablets completely
before swallowing.

Bubble Gum
Flavor

24 Chewable
Tablets

Actual Tablet Size

TAMPER EVIDENT: DO NOT USE IF IMPRINTED
SAFETY SEAL UNDER CAP IS BROKEN OR MISSING

*This product is not manufactured or distributed
by The Procter & Gamble Company, owner of the
registered trademark Pepto® Kids Chewables.
50844 ORG111959608

DISTRIBUTED BY
OLD EAST MAIN CO.
100 MISSION RIDGE
GOODLETTSVILLE, TN 37072

100%
Satisfaction
Guaranteed!
(888) 309-9030

Dollar General 44-596A